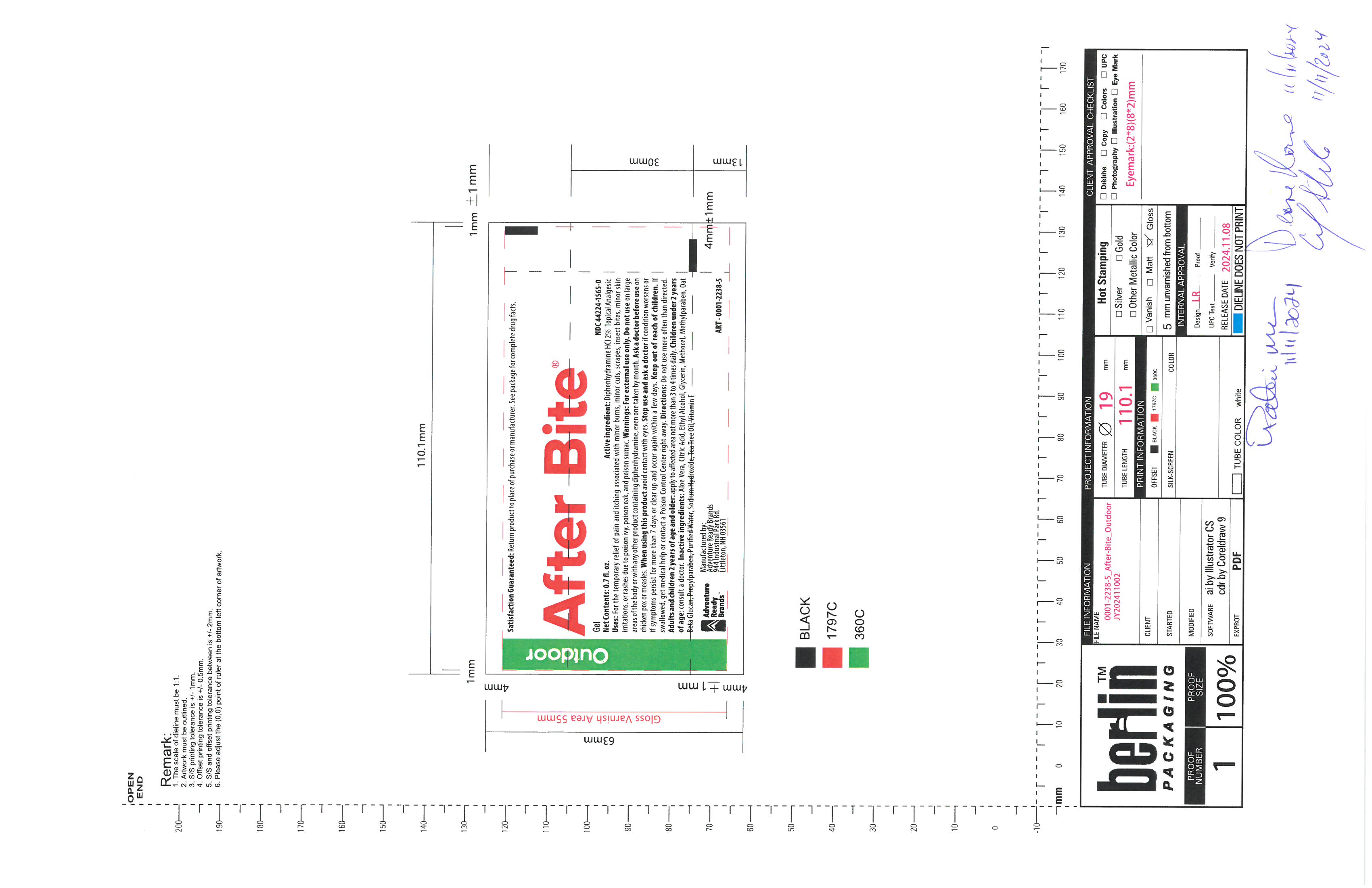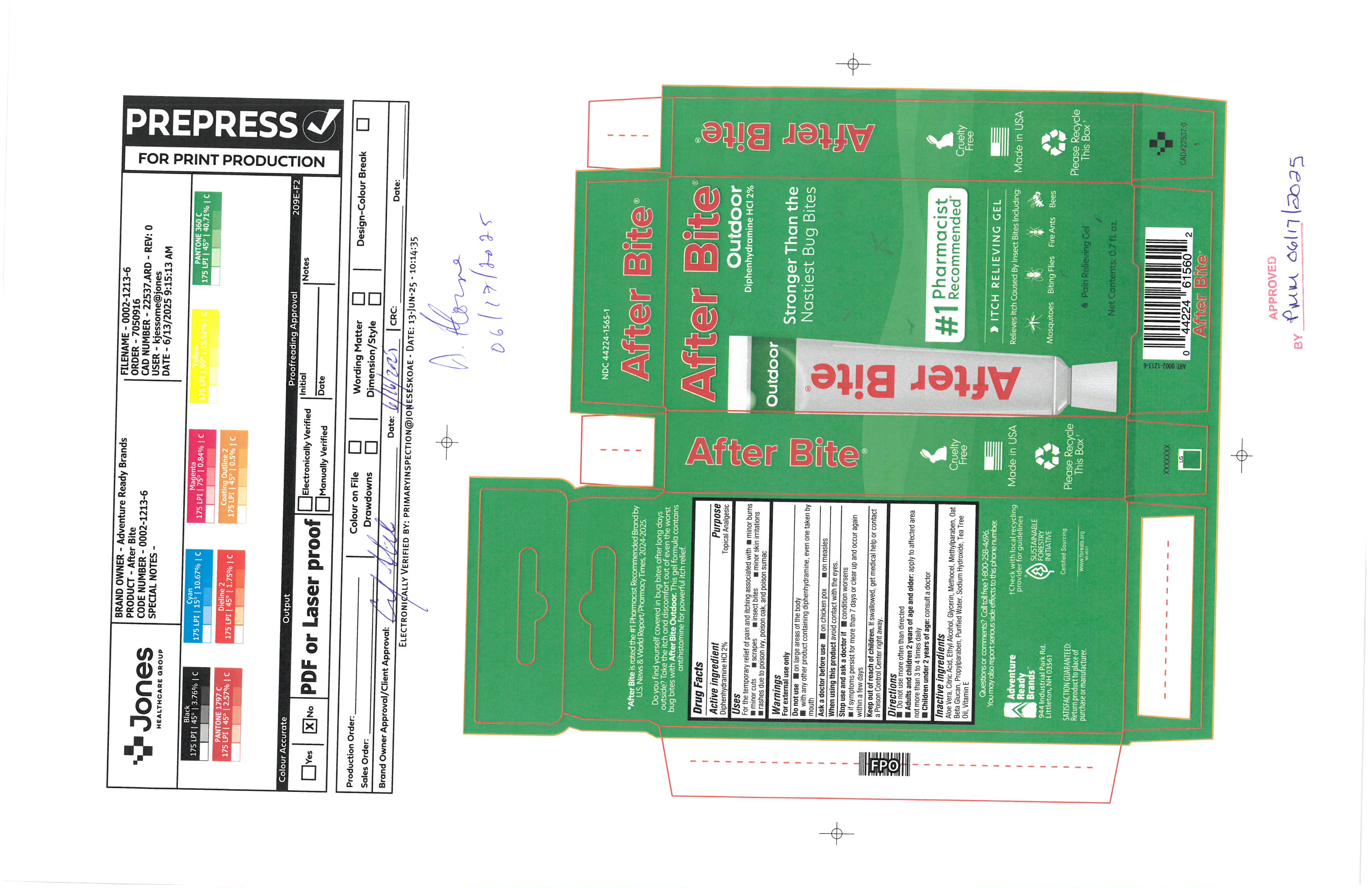 DRUG LABEL: After Bite Outdoor
NDC: 44224-1565 | Form: GEL
Manufacturer: Tender Corporation d/b/a Adventure Ready Brands
Category: otc | Type: HUMAN OTC DRUG LABEL
Date: 20251114

ACTIVE INGREDIENTS: DIPHENHYDRAMINE HYDROCHLORIDE 0.4 g/20 g
INACTIVE INGREDIENTS: TEA TREE OIL 0.1 g/20 g; WATER 12.12 g/20 g; ANHYDROUS CITRIC ACID 0.044 g/20 g; ALOE VERA LEAF 0.82 g/20 g; METHYLPARABEN 0.04 g/20 g; SODIUM HYDROXIDE 0.26 g/20 g; ALCOHOL 5.2 g/20 g; PROPYLPARABEN 0.02 g/20 g; HYPROMELLOSE, UNSPECIFIED 0.4 g/20 g; GLYCERIN 0.8 g/20 g; OAT 0.2 g/20 g; .ALPHA.-TOCOPHEROL ACETATE 0.06 g/20 g

After Bite Outdoor

Active Ingredient

Diphenhydramine HCl 2%

Purpose

Topical Analgesic

Uses

For temporary relief of pain and itching associated with, minor burns, minor cuts, scrapes, insect bites, minor skin irritations, rashes due to poison ivy, poison oak, and poison sumac.

Warnings

For external use only

Do not use

on large areas of the body, with any other product containing diphenhydramine, even one taken by mouth.

Ask a doctor before use

On chicken pox, on measles

when using this product

Avoid contact with eyes.

Stop use and ask a doctor if

Condition worsens, if symptoms persist more than 7 days or clear up and occur again within a few days

Keep out of reach of children

If swallowed, get medical help or contact a Posion Control Center right away.

Directions

Do not use more often than directed, Adults and children 2 years of age and older: Apply to affected area not more than 3 to 4 times daily.

Children under 2 year of age consult a doctor

Inactive Ingredients

Aloe Vera, Citric Acide, Ethyl Alcohol, Glycerin, Methocel, methylparaben, oat beta glucan, propylparaben, purified water, sodium hydroxide, tea tree oil, vitamine e